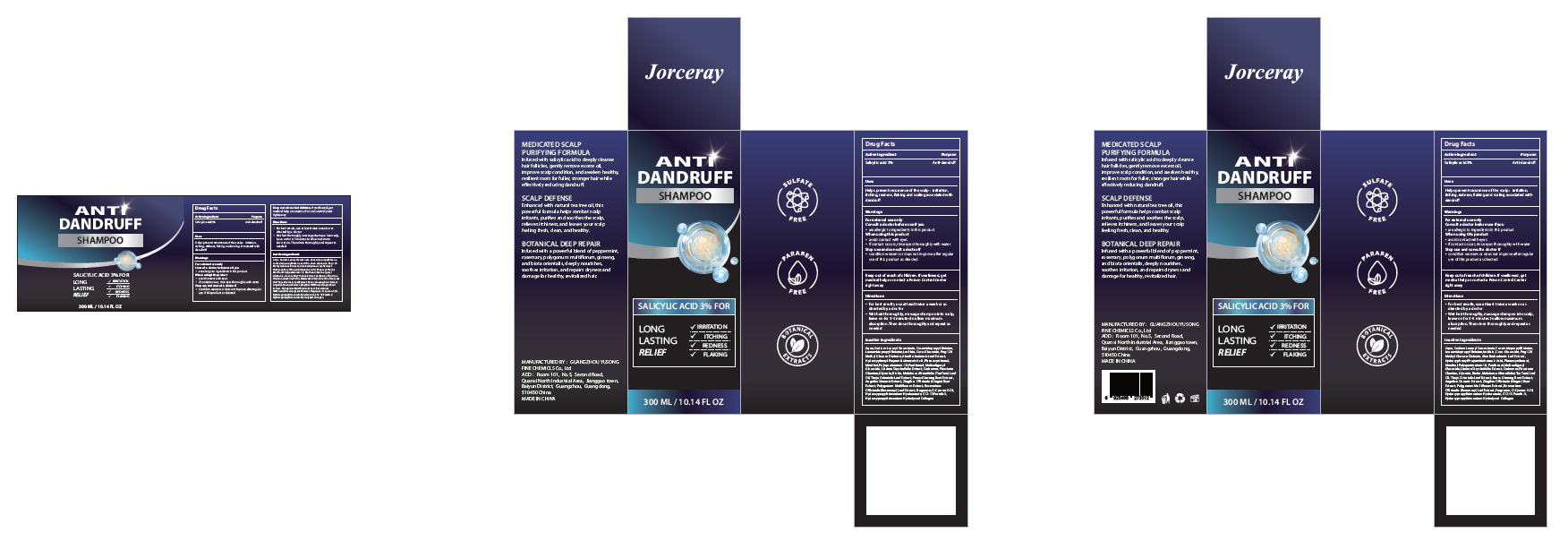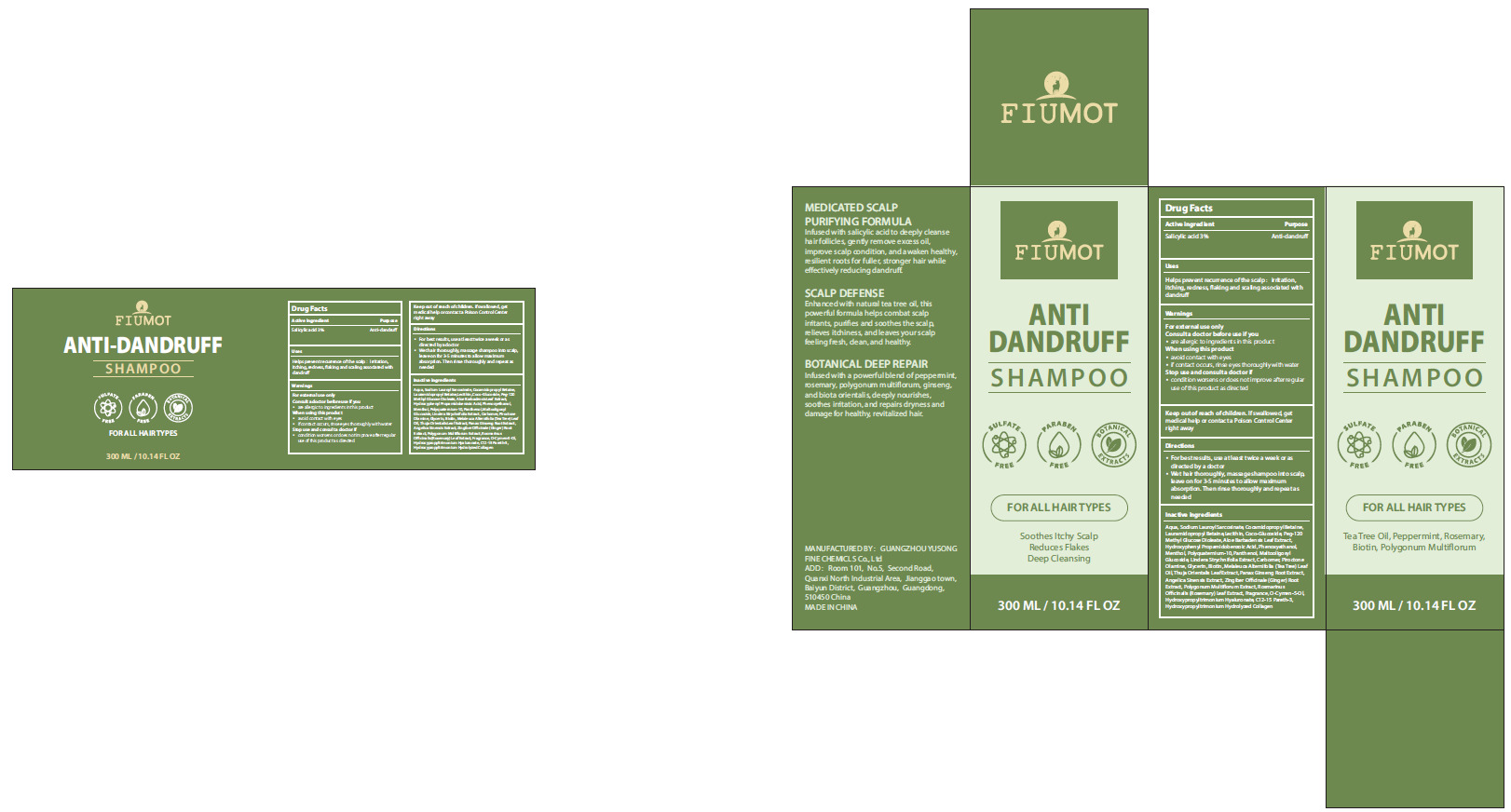 DRUG LABEL: anti-dandruff
NDC: 84558-010 | Form: SHAMPOO
Manufacturer: GUANGZHOU YUSONG FINE CHEMICLS Co., Ltd
Category: otc | Type: HUMAN OTC DRUG LABEL
Date: 20250709

ACTIVE INGREDIENTS: SALICYLIC ACID 3 g/100 mL
INACTIVE INGREDIENTS: LECITHIN, SUNFLOWER; COCO-GLUCOSIDE; AQUA; CARBOMER; PIROCTONE OLAMINE; C12-15 PARETH-3; SODIUM LAUROYL SARCOSINATE; COCAMIDOPROPYL BETAINE; LAURAMIDOPROPYL BETAINE; MENTHOL; O-CYMEN-5-OL; PEG-120 METHYL GLUCOSE DIOLEATE; MELALEUCA ALTERNIFOLIA (TEA TREE) LEAF OIL; POLYQUATERNIUM-10 (125 MPA.S AT 2%); HYDROXYPHENYL PROPAMIDOBENZOIC ACID; PHENOXYETHANOL; PANTHENOL; MALTOOLIGOSYL GLUCOSIDE; GLYCERIN; BIOTIN; PLATYCLADUS ORIENTALIS LEAF; ROSMARINUS OFFICINALIS (ROSEMARY) LEAF POWDER; FRAGRANCE 13576; ALOE BARBADENSIS LEAF; PANAX GINSENG ROOT; GINGER

84558-010

Active Ingredient(s)

Salicylic acid 3%

Purpose

Anti-dandruff

Use

Helps prevent recurrence of the scalp: irritation,
itching, redness, flaking and scaling associated with
dandruff

Warnings

For external use only
Consult a doctor before use if you
■ are allergic to ingredients in this product
When using this product
■ avoid contact with eyes
■ if contact occurs, rinse eyes thoroughly with water
Stop use and consult a doctor if
■ condition worsens or does not improve after regular use of this product as directed

Do not use if allergic to the ingredients in this product

WHEN USING

1. avoid contact with eyes
2. if contact occurs, rinse eyes thoroughly with water

STOP USE

condition worsens or does not improve after regular use of this product as directed

Keep out of reach of children. If swallowed, get medical help or contact a Poison Control Center
right away

Directions

1. For best results, use at least twice a week or as directed by a doctor
2. Wet hair thoroughly, massage shampoo into scalp, leave on for 3-5 minutes to allow maximum
absorption. Then rinse thoroughly and repeat as needed

Other information

No Data

Inactive ingredients

Aqua, Sodium Lauroyl Sarcosinate, Cocamidopropyl Betaine, Lauramidopropyl Betaine,Lecithin, Coco-Glucoside, Peg-120
MethyI Glucose Dioleate, Aloe Barbadensis Leaf Extract, HydroxyphenyI Propamidobenzoic Acid, Phenoxyethanol,
Menthol, Polyquaternium 10, Panthenol, Maltooligosyl Glucoside, Lindera Strychnifolia Extract, Carbomer, Piroctone
Olamine, Glycerin, Biotin, Melaleuca Alternifolia (Tea Tree) Leaf Oil, Thuja Orientalis Leaf Extract, Panax Ginseng Root Extract,
Angelica Sinensis Extract, Zingiber Officinale (Ginger) Root Extract, Polygonum Multiflorum Extract, Rosmarinus
Officinalis (Rosemary) Leaf Extract, Fragrance, O-Cymen-5-Ol, Hydroxypropyltrimonium Hyaluronate, C12-15 Pareth-3,
Hydroxypropyltrimonium Hydrolyzed Collagen